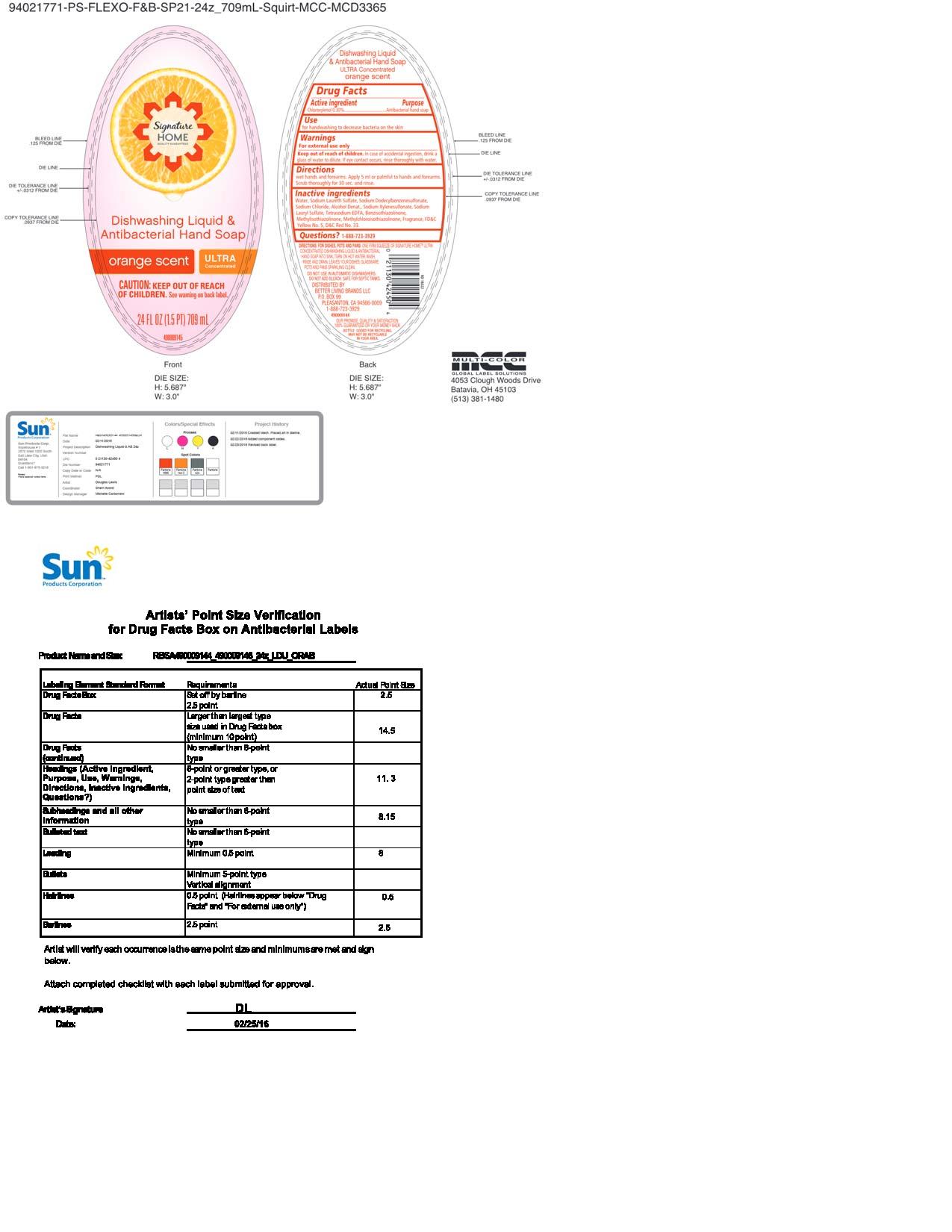 DRUG LABEL: Signature Home AB Orange
NDC: 63691-027 | Form: SOAP
Manufacturer: Sun Products Corporation
Category: otc | Type: HUMAN OTC DRUG LABEL
Date: 20160629

ACTIVE INGREDIENTS: CHLOROXYLENOL 0.3 g/100 mL
INACTIVE INGREDIENTS: SODIUM XYLENESULFONATE; SODIUM LAURYL SULFATE; SODIUM LAURETH SULFATE; ALCOHOL; EDETATE SODIUM; METHYLCHLOROISOTHIAZOLINONE; FD&C YELLOW NO. 5; D&C RED NO. 33; WATER; BENZISOTHIAZOLINONE; METHYLISOTHIAZOLINONE; SODIUM DODECYLBENZENESULFONATE; SODIUM CHLORIDE

Dishwashing Liquid & Antibacterial Hand Soap

ULTRA Concentrated

orange scent

Active Ingredient

Chloroxylenol 0.30%

Purpose

Antibacterial hand soap

Use

for handwashing to decrease bacteria on the skin

Warnings

For external use only

.

Keep out of reach of children

In case of accidental ingestion, drink a glass of water to dilute. If eye contact occurs, rinse thoroughly with water.

Directions

wet hands and forearms. Apply 5 ml or palmful to hands and forearms. Scrub thoroughly for 30 sec. and rinse.

Inactive ingredients

Water, Sodium Laureth Sulfate, Sodium Didecylbenzenesulfonate, Sodium Chloride, Alcohol Denat., Sodium Xylenesulfonate, Sodium Lauryl Sulfate, Tetrasodium EDTA, Benzisothiazolinone, Methylisothiazolinone, Methylchloroisothiazolinone, Fragrance, FD&C Yello No. 5, D&C Red No. 33

Questions?

Questions? 1-888-723-3929